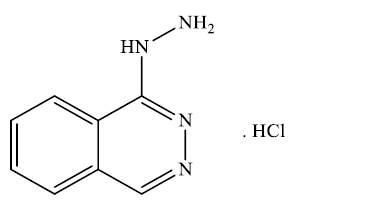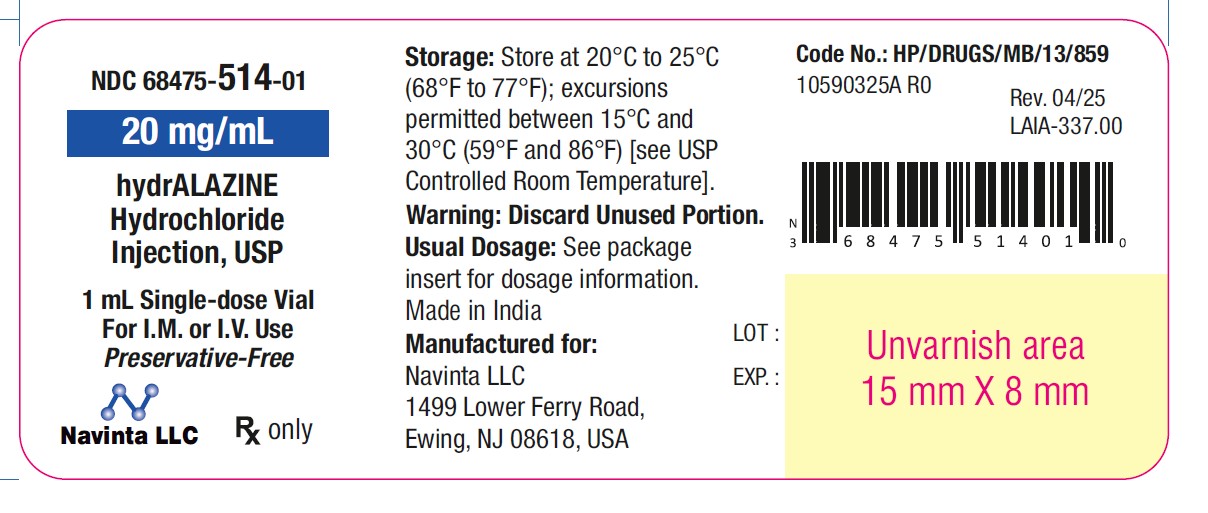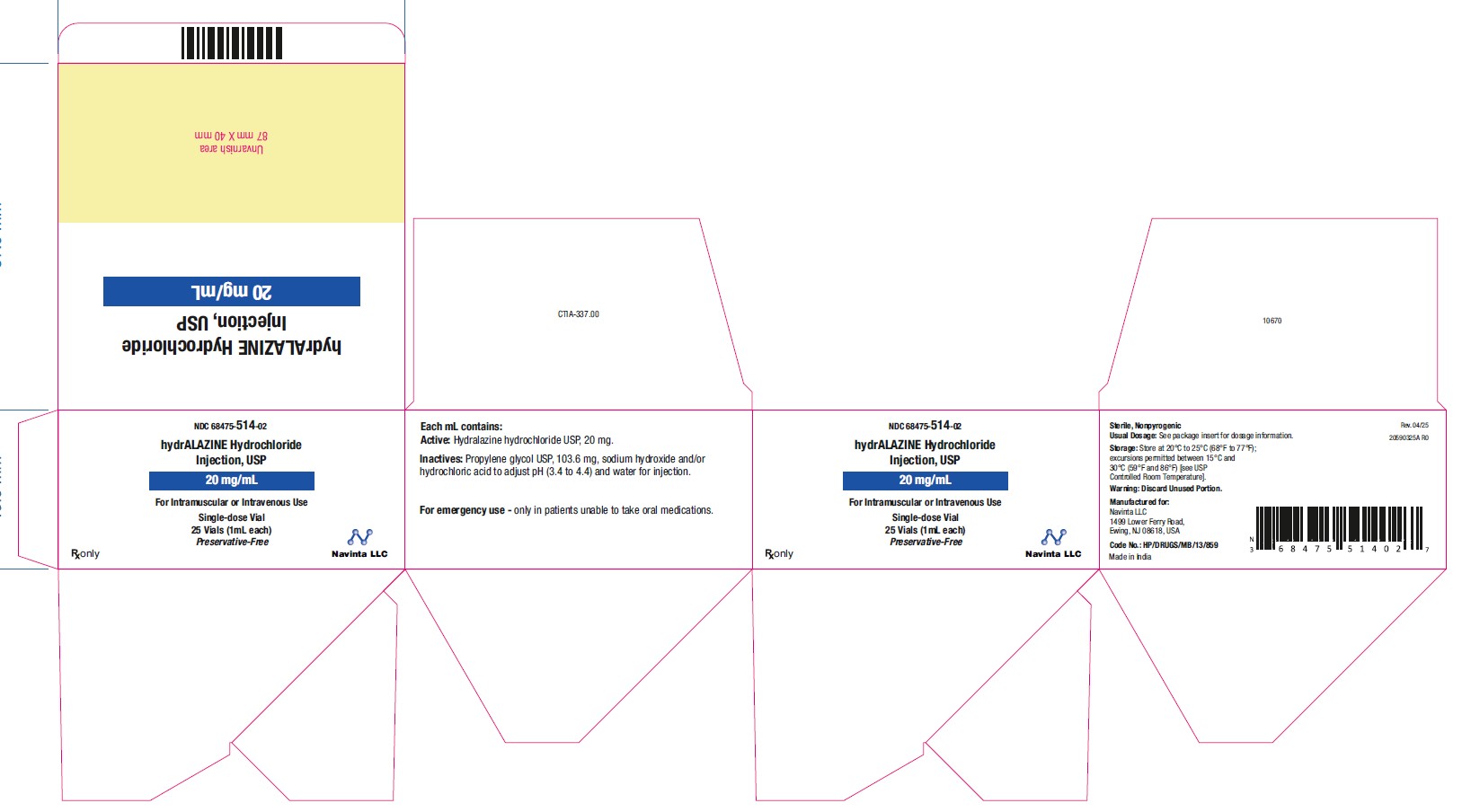 DRUG LABEL: Hydralazine Hydrochloride
NDC: 68475-514 | Form: INJECTION
Manufacturer: Navinta LLC
Category: prescription | Type: HUMAN PRESCRIPTION DRUG LABEL
Date: 20251125

ACTIVE INGREDIENTS: HYDRALAZINE HYDROCHLORIDE 20 mg/1 mL
INACTIVE INGREDIENTS: HYDROCHLORIC ACID; PROPYLENE GLYCOL; SODIUM HYDROXIDE; WATER

Hydralazine Hydrochloride Injection, USP
Preservative Free
Rx only

DESCRIPTION

Hydralazine hydrochloride injection, USP is an antihypertensive available in a 1 mL vial for intravenous and intramuscular administration. Hydralazine hydrochloride injection, USP is a sterile, nonpyrogenic clear, colorless solution.

Each mL contains:

Active: Hydralazine hydrochloride USP, 20 mg

Preservative Free Formulation

Inactives: Propylene glycol USP, 103.6 mg; sodium hydroxide and/or hydrochloric acid USP to adjust pH (3.4 to 4.4) and water for injection.

Hydralazine hydrochloride USP is 1-hydrazinophthalazine monohydrochloride, and its structural formula is:

Molecular Formula C8H8N4•HCl

Hydralazine hydrochloride USP is a white to off-white, odorless crystalline powder. It is soluble in water, slightly soluble in alcohol, and very slightly soluble in ether. It melts at about 288.90°C, with decomposition, and has a molecular weight of 196.64.

CLINICAL PHARMACOLOGY

Although the precise mechanism of action of hydralazine is not fully understood, the major effects are on the cardiovascular system. Hydralazine apparently lowers blood pressure by exerting a peripheral vasodilating effect through a direct relaxation of vascular smooth muscle. Hydralazine, by altering cellular calcium metabolism, interferes with the calcium movements within the vascular smooth muscle that are responsible for initiating or maintaining the contractile state.

The peripheral vasodilating effect of hydralazine results in decreased arterial blood pressure (diastolic more than systolic), decreased peripheral vascular resistance, and an increased heart rate, stroke volume, and cardiac output. The preferential dilatation of arterioles, as compared to veins, minimizes postural hypotension and promotes the increase in cardiac output. Hydralazine usually increases renin activity in plasma, presumably as a result of increased secretion of renin by the renal juxtaglomerular cells in response to reflex sympathetic discharge. This increase in renin activity leads to the production of angiotensin II, which then causes stimulation of aldosterone and consequent sodium reabsorption. Hydralazine also maintains or increases renal and cerebral blood flow.

The average maximal decrease in blood pressure usually occurs 10 to 80 minutes after administration of hydralazine hydrochloride injection. No other pharmacokinetic data on hydralazine hydrochloride injection are available.

INDICATIONS AND USAGE

Severe essential hypertension when the drug cannot be given orally or when there is an urgent need to lower blood pressure.

CONTRAINDICATIONS

Hypersensitivity to hydralazine; coronary artery disease; mitral valvular rheumatic heart disease.

WARNINGS

In a few patients hydralazine may produce a clinical picture simulating systemic lupus erythematosus including glomerulonephritis. In such patients hydralazine should be discontinued unless the benefit-to-risk determination requires continued antihypertensive therapy with this drug. Symptoms and signs usually regress when the drug is discontinued but residua have been detected many years later. Long-term treatment with steroids may be necessary (see PRECAUTIONS, Laboratory Tests).

PRECAUTIONS

General: Myocardial stimulation produced by hydralazine can cause anginal attacks and ECG changes of myocardial ischemia. The drug has been implicated in the production of myocardial infarction. It must, therefore, be used with caution in patients with suspected coronary artery disease.

The "hyperdynamic" circulation caused by hydralazine may accentuate specific cardiovascular inadequacies. For example, hydralazine may increase pulmonary artery pressure in patients with mitral valvular disease. The drug may reduce the pressor responses to epinephrine. Postural hypotension may result from hydralazine but is less common than with ganglionic blocking agents. It should be used with caution in patients with cerebral vascular accidents.

In hypertensive patients with normal kidneys who are treated with hydralazine, there is evidence of increased renal blood flow and a maintenance of glomerular filtration rate. In some instances where control values were below normal, improved renal function has been noted after administration of hydralazine. However, as with any antihypertensive agent, hydralazine should be used with caution in patients with advanced renal damage.

Peripheral neuritis, evidenced by paresthesia, numbness, and tingling, has been observed. Published evidence suggests an antipyridoxine effect, and that pyridoxine should be added to the regimen if symptoms develop.

Laboratory Tests: Complete blood counts and antinuclear antibody titer determinations are indicated before and periodically during prolonged therapy with hydralazine even though the patient is asymptomatic. These studies are also indicated if the patient develops arthralgia, fever, chest pain, continued malaise, or other unexplained signs or symptoms.

A positive antinuclear antibody titer requires that the physician carefully weigh the implications of the test results against the benefits to be derived from antihypertensive therapy with hydralazine hydrochloride.

Blood dyscrasias, consisting of reduction in hemoglobin and red cell count, leukopenia, agranulocytosis, and purpura, have been reported. If such abnormalities develop, therapy should be discontinued.

Drug Interactions: MAO inhibitors should be used with caution in patients receiving hydralazine.

When other potent parenteral antihypertensive drugs, such as diazoxide, are used in combination with hydralazine, patients should be continuously observed for several hours for any excessive fall in blood pressure. Profound hypotensive episodes may occur when diazoxide injection and hydralazine injection are used concomitantly.

Carcinogenesis, Mutagenesis, Impairment of Fertility: In a lifetime study in Swiss albino mice, there was a statistically significant increase in the incidence of lung tumors (adenomas and adenocarcinomas) of both male and female mice given hydralazine continuously in their drinking water at a dosage of about 250 mg/kg per day (about 80 times the maximum recommended human dose). In a 2-year carcinogenicity study of rats given hydralazine by gavage at dose levels of 15, 30, and 60 mg/kg/day (approximately 5 to 20 times the recommended human daily dosage), microscopic examination of the liver revealed a small, but statistically significant, increase in benign neoplastic nodules in male and female rats from the high-dose group and in female rats from the intermediate-dose group. Benign interstitial cell tumors of the testes were also significantly increased in male rats from the high-dose group. The tumors observed are common in aged rats and a significantly increased incidence was not observed until 18 months of treatment. Hydralazine was shown to be mutagenic in bacterial systems (Gene Mutation and DNA Repair) and in one of two rats and one rabbit hepatocyte in vitro DNA repair studies. Additional in vivo and in vitro studies using lymphoma cells, germinal cells, and fibroblasts from mice, bone marrow cells from chinese hamsters and fibroblasts from human cell lines did not demonstrate any mutagenic potential for hydralazine.

The extent to which these findings indicate a risk to man is uncertain. While long-term clinical observation has not suggested that human cancer is associated with hydralazine use, epidemiologic studies have so far been insufficient to arrive at any conclusions.

Pregnancy: Teratogenic effects. Animal studies indicate that hydralazine is teratogenic in mice at 20 to 30 times the maximum daily human dose of 200 to 300 mg and possibly in rabbits at 10 to 15 times the maximum daily human dose, but that it is nonteratogenic in rats. Teratogenic effects observed were cleft palate and malformations of facial and cranial bones.

There are no adequate and well-controlled studies in pregnant women. Although clinical experience does not include any positive evidence of adverse effects on the human fetus, hydralazine should be used during pregnancy only if the expected benefit justifies the potential risk to the fetus.

Nursing Mothers: Hydralazine has been shown to be excreted in breast milk.

Pediatric Use: Safety and effectiveness in pediatric patients have not been established in controlled clinical trials, although there is experience with the use of hydralazine hydrochloride in children. The usual recommended parenteral dosage, administered intramuscularly or intravenously, is 1.7 to 3.5 mg/kg of body weight daily, divided into four to six doses.

ADVERSE REACTIONS

Adverse reactions with hydralazine hydrochloride are usually reversible when dosage is reduced. However, in some cases it may be necessary to discontinue the drug.

The following adverse reactions have been observed, but there has not been enough systematic collection of data to support an estimate of their frequency.

Common: | Headache, anorexia, nausea, vomiting, diarrhea, palpitations, tachycardia, angina pectoris.
Less Frequent: | Digestive: constipation, paralytic ileus. Cardiovascular: hypotension, paradoxical pressor response, edema. Respiratory: dyspnea. Neurologic: peripheral neuritis, evidenced by paresthesia, numbness, and tingling; dizziness; tremors; muscle cramps; psychotic reactions characterized by depression, disorientation, or anxiety. Genitourinary: difficulty in urination. Hematologic: blood dyscrasias, consisting of reduction in hemoglobin and red cell count, leukopenia, agranulocytosis, purpura; lymphadenopathy; splenomegaly. Hypersensitive Reactions: rash, urticaria, pruritus, fever, chills, arthralgia, eosinophilia, and, rarely, hepatitis. Other: nasal congestion, flushing, lacrimation, conjunctivitis.

OVERDOSAGE

Acute Toxicity: | No deaths due to acute poisoning have been reported. Highest known dose survived: adults, 10 g orally. Oral LD50 in rats: 173 and 187 mg/kg.

Signs and Symptoms: Signs and symptoms of overdosage include hypotension, tachycardia, headache, and generalized skin flushing.

Complications can include myocardial ischemia and subsequent myocardial infarction, cardiac arrhythmia, and profound shock.

Treatment: There is no specific antidote.

Support of the cardiovascular system is of primary importance. Shock should be treated with plasma expanders. If possible, vasopressors should not be given, but if a vasopressor is required, care should be taken not to precipitate or aggravate cardiac arrhythmia. Tachycardia responds to beta blockers. Digitalization may be necessary, and renal function should be monitored and supported as required.

No experience has been reported with extracorporeal or peritoneal dialysis.

DOSAGE AND ADMINISTRATION

When there is urgent need, therapy in the hospitalized patient may be initiated intramuscularly or as a rapid intravenous bolus injection directly into the vein. Hydralazine hydrochloride injection should be used only when the drug cannot be given orally. The usual dose is 20 to 40 mg, repeated as necessary.

Certain patients (especially those with marked renal damage) may require a lower dose. Blood pressure should be checked frequently. It may begin to fall within a few minutes after injection, with the average maximal decrease occurring in 10 to 80 minutes. In cases where there has been increased intracranial pressure, lowering the blood pressure may increase cerebral ischemia. Most patients can be transferred to oral hydralazine hydrochloride within 24 to 48 hours.

The product should be used immediately after the vial is opened. It should not be added to infusion solutions. Hydralazine hydrochloride injection may discolor upon contact with metal; discolored solutions should be discarded.

Parenteral drug products should be inspected visually for particulate matter and discoloration prior to administration, whenever solution and container permit.

HOW SUPPLIED

Hydralazine hydrochloride injection USP, 20 mg/mL is supplied as follows:

NDC 68475-514-01 | 1 mL Single-dose Vial
NDC 68475-514-02 | 1 mL Single-dose Vial | Packaged in boxes of 25

Storage: Store at 20°C to 25°C (68°F to 77°F); excursions permitted between 15°C and 30°C (59°F and 86°F) [see USP Controlled Room Temperature].

Manufactured for:

Navinta LLC

1499 Lower Ferry Road,

Ewing, NJ 08618, USA

Made in India

30590325 R0

April 2025

PRINCIPAL DISPLAY PANEL - Vial

NDC 68475-514-01

20 mg/mL

hydrALAZINE

Hydrochloride

Injection, USP

1 mL Single-dose Vial

For I.M or I.V Use

Preservative-Free

Navinta LLC

Rx only

PRINCIPAL DISPLAY PANEL - Carton

NDC 68475-514-02

hydrALAZINE Hydrochloride

Injection, USP

20 mg/mL

For Intramuscular or Intravenous Use

Single-dose Vial

25 Vial (1mL each)

Preservative-Free

Navinta LLC

Rx Only